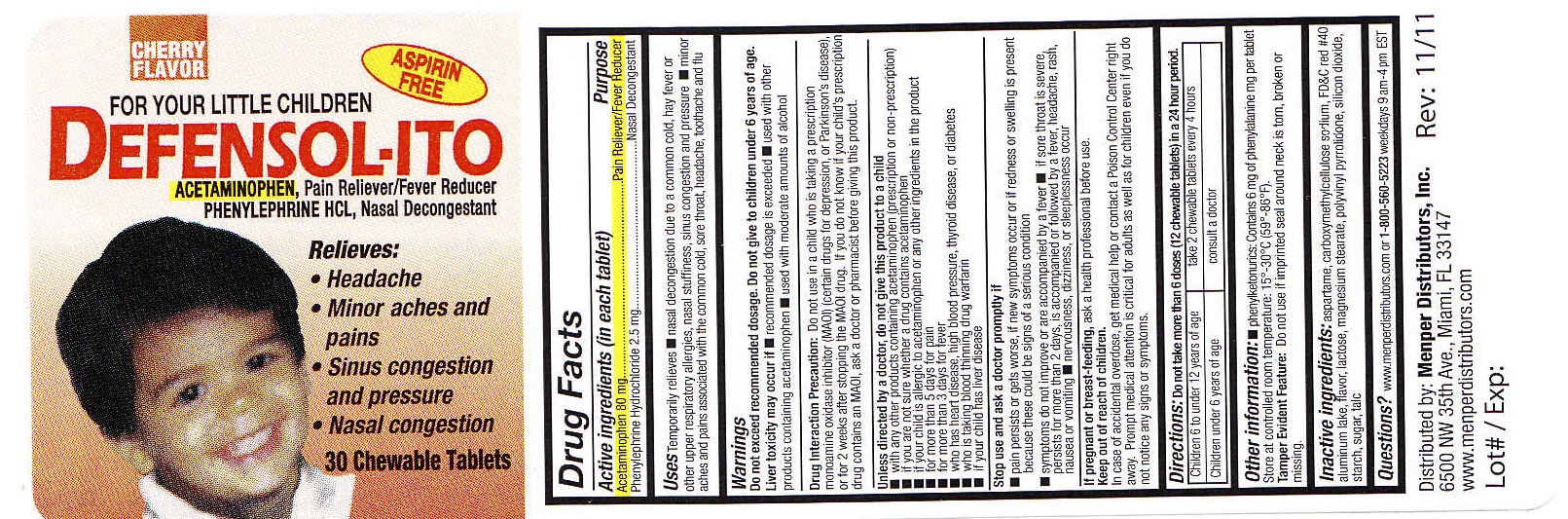 DRUG LABEL: Defensolito
NDC: 53145-006 | Form: TABLET, CHEWABLE
Manufacturer: Menper Distributors, Inc.
Category: otc | Type: HUMAN OTC DRUG LABEL
Date: 20250722

ACTIVE INGREDIENTS: ACETAMINOPHEN 80 mg/1 1; PHENYLEPHRINE HYDROCHLORIDE 2.5 mg/1 1
INACTIVE INGREDIENTS: ASPARTAME; CARBOXYMETHYLCELLULOSE SODIUM; LACTOSE; MAGNESIUM STEARATE; POLYVINYL ACETATE PHTHALATE; SILICON DIOXIDE; STARCH, CORN; SUGARCANE; TALC

Defensol-ito

Active ingredients (in each tablet)
Acetaminophen 80 mg

Phenylephrine Hydrochloride 2.5 mg

Purpose

Pain reliever/ Fever Reducer

Nasal Decongestant

Uses

Temporarily relieves

- nasal decongestion due to a common cold, hay fever or other upper respiratory allergies, nasal stuffiness, sinus congestion and pressure
- minor aches and pains associated with the common cold, sore throat, headache, tootheache and flu

Warnings

Do not exceed recommended dosage. Do not give to children under 6 years of age.

Liver toxicity may occur if

- recommended dosage is exceeded
- used with other products containing acetaminophen
- used with moderate amounts of alcohol

Drug Interaction Precaution: Do not use in a child who is taking prescription monoamine oxidase inhibitor (MAOI) (certain drugs for depression, or Parkinson's Disease), or for two weeks after stopping the MAOI drug. If you do not know if your child's prescription drug contains an MAOI, ask a doctor or pharmacist before giving this product.

DO NOT USE

Do not give this product to a child unless directed by a doctor:

- with any other products containing acetaminophen (prescription or non-prescription)
- if you are not sure whether a drug contains acetaminophen
- if your child is allergic to acetaminophen or any other ingredients in the product
- for more than 5 days for pain
- for more than 3 days for fever
- who has heart disease, high blood pressure, thyroid disease, or diabetes
- who is taking blood thinning drug warfarin
- if your child has liver disease

Stop use and ask doctor promptly if

- pain persists and gets worse, if new symptoms occur or if redness or swelling is present because these could be signs of a serious condition
- symptoms do not improve or are accompanied by a fever
- if sore throat is severe, persists for more than 2 days, is accompanied or followed by a fever, headache, rash, nausea or vomiting
- nervousness, dizziness, or sleeplessness occur

PREGNANCY OR BREAST FEEDING

If pregnant or breast feeding,ask a health care professional before use.

Keep out of reach of children.

OVERDOSAGE

In case of overdose, get medical help or contact a Poison Control Center right away.

Prompt medical attention is critical for adults as well as children even if you do not notice any signs or symptoms

Directions

- Do not take more than 6 doses (12 chewable tablets) in a 24 hour period

Children 6 to under 12 years of age | take 2 chewable tablets every 4 hours
Children under 6 years of age | consult a doctor

INACTIVE INGREDIENT

Inactive IngredientsAspartame, Carboxymethylcellulose Sodium, FD&C #40 aluminum lake, Flavor, Lactose, Magnesium Stearate, Polyvinyl Pirrolidone, Silicon Dioxide, Starch, Sugar and Talc.

QUESTIONS

Questions?Call 1-800-560-5223 weekdays 9 AM-4 PM EST